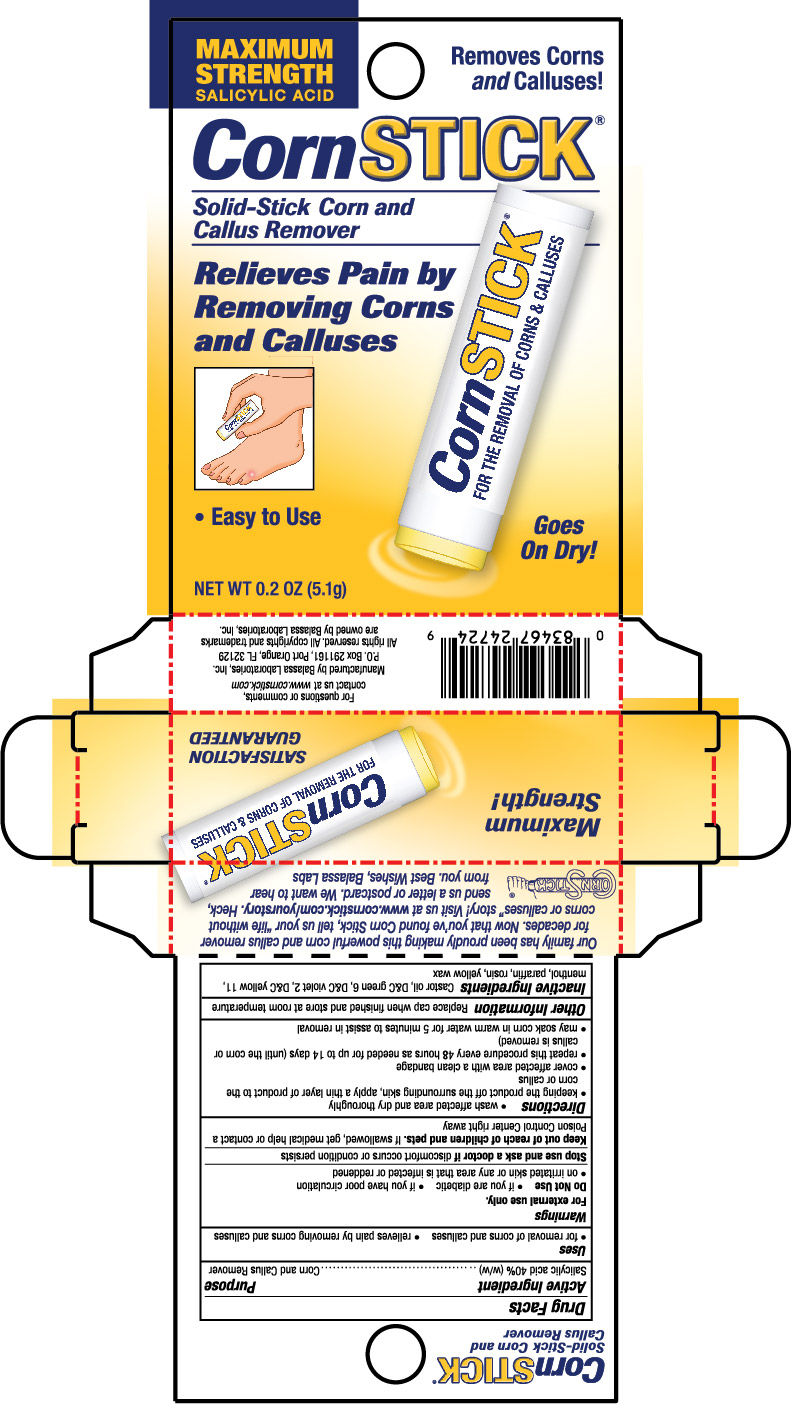 DRUG LABEL: CornStick
NDC: 10107-240 | Form: STICK
Manufacturer: Balassa Laboratories Inc.
Category: otc | Type: HUMAN OTC DRUG LABEL
Date: 20241001

ACTIVE INGREDIENTS: SALICYLIC ACID 0.4 g/1 g
INACTIVE INGREDIENTS: CASTOR OIL; MENTHOL; YELLOW WAX; PARAFFIN; ROSIN; D&C GREEN NO. 6; D&C VIOLET NO. 2; D&C YELLOW NO. 11

CornStick Corn and Callus Remover

Active Ingredient

Salicylic acid 40% (w/w)

Purpose

Corn and Callus Remover

Uses

- for removal of corns and calluses.
- relieves pain by removing corns and calluses.

Warnings

For external use only.

Do not use

- if you are diabetic
- if you have poor circulation
- on irritated skin or any area that is infected or reddened

Stop use and ask a doctor if

discomfort occurs or condition persists

Keep out of reach of children and pets.

If swallowed, get medical help or contact a Poison Control Center right away.

Directions

- wash affected area and dry thoroughly
- keeping the product off the surrounding skin, apply thin layer of product to the corn or callus
- cover affected area with a clean bandage
- repeat this procedure every 48 hours as needed for up to 14 days (until the corn or callus is removed)
- may soak corn in warm water for 5 minutes to assist in removal

Other Information

Replace cap when finished and store at room temperature

Inactive Ingredients

Castor oil, D&C green 6, D&C violet 2, D&C yellow 11, menthol, paraffin, rosin, yellow wax

PRINCIPAL DISPLAY PANEL - 5.1 g Tube in Carton

MAXIMUM STRENGTH SALICYLIC ACID

Removes Corns andCalluses!

CornSTICK ®

Solid-Stick Corn Remover and Callus Remover

Relieves Pain by Removing Corns and Calluses

- Easy to Use

Goes On Dry!

NET WT 0.2 OZ (5.1g)